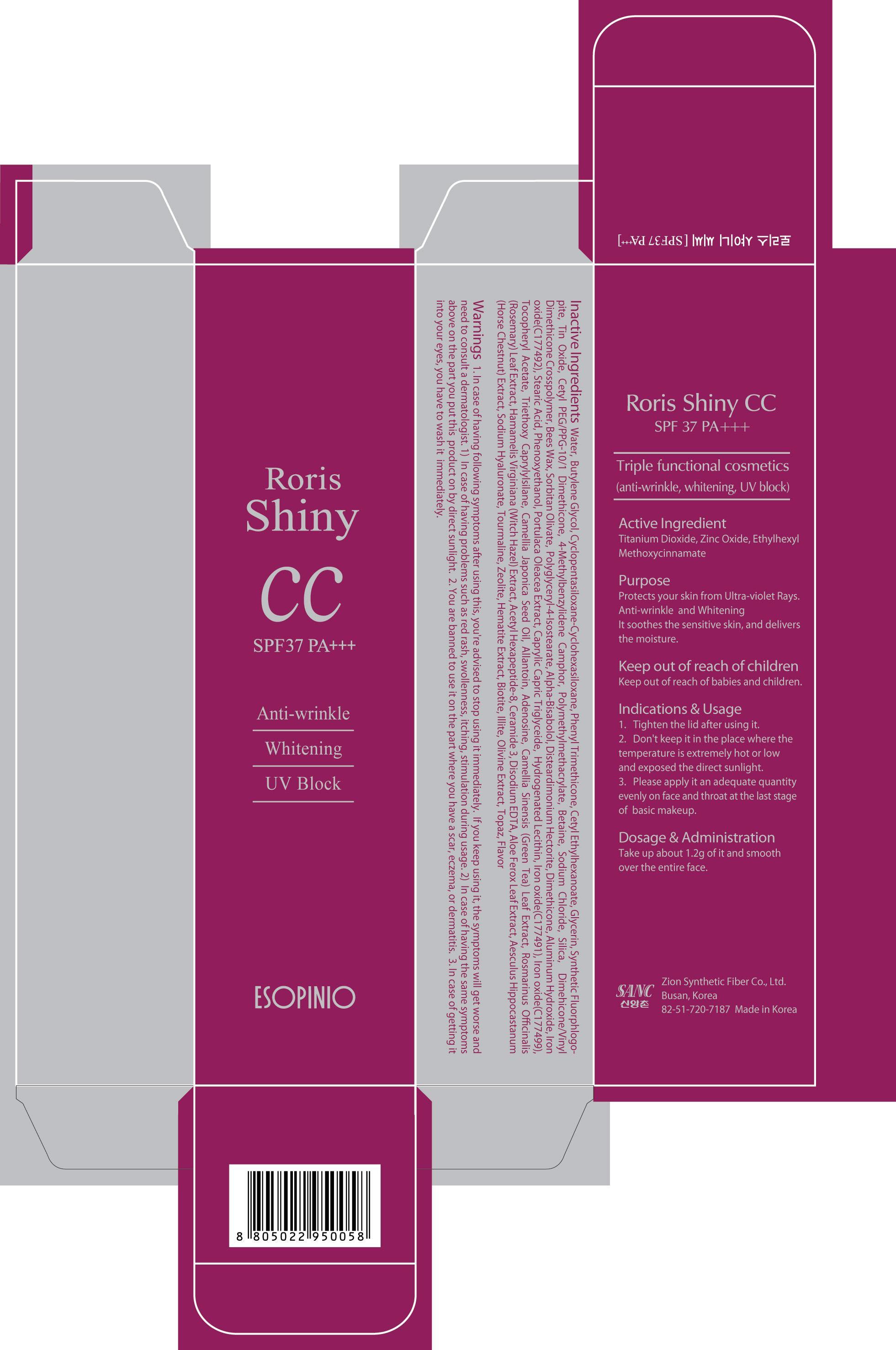 DRUG LABEL: RORIS SHINY CC
NDC: 44781-220 | Form: CREAM
Manufacturer: ZION SYNTHETIC FIBER CO., LTD.
Category: otc | Type: HUMAN OTC DRUG LABEL
Date: 20130506

ACTIVE INGREDIENTS: Titanium Dioxide 4.87 g/50 g; OCTINOXATE 3.75 g/50 g; Zinc Oxide 1.5 g/50 g
INACTIVE INGREDIENTS: Water; Butylene Glycol; Glycerin

ACTIVE INGREDIENT

Active Ingredients: Titanium Dioxide, Zinc Oxide, Ethylhexyl Methoxycinnamate

INACTIVE INGREDIENT

Inactive Ingredients:
Water, Butylene Glycol, Cyclopentasiloxane-Cyclohexasiloxane, Phenyl Trimethicone, Cetyl Ethylhexanoate, Glycerin, Synthetic Fluorphlogopite, Tin Oxide, Cetyl PEG/PPG-10/1, Dimethicone, 4-Methylbenzylidene Camphor, Polymethylmethacrylate, Betaine,
Sodium Chloride, Silica, Dimehicone/Vinyl Dimethicone Crosspolymer, Bees Wax, Sorbitan Olivate, Polyglyceryl-4-Isostearate, Alpha-Bisabolol, Disteardimonium Hectorite, Dimethicone, Aluminum Hydroxide, Iron oxide(C177492), Stearic Acid, Phenoxyethanol,
Portulaca Oleacea Extract, Caprylic Capric Triglyceide, Hydrogenated Lecithin, Iron oxide, (C177491), Iron oxide(C177499), Tocopheryl Acetate, Triethoxy Caprylylsilane, Camellia, Japonica Seed Oil, Allantoin, Adenosine, Camellia Sinensis (Green Tea) Leaf Extract,
Rosmarinus Officinalis (Rosemary) Leaf Extract, Hamamelis Virginiana (Witch Hazel) Extract, Acetyl Hexapeptide-8, Ceramide 3, Disodium EDTA, Aloe Ferox Leaf Extract, Aesculus Hippocastanum (Horse Chestnut) Extract, Sodium Hyaluronate, Tourmaline,
Zeolite, Hematite Extract, Biotite, Illite, Olivine Extract, Topaz, Flavor

PURPOSE

Protects your skin from Ultra-violet Rays.
Anti-wrinkle and Whitening
It soothes the sensitive skin, and delivers the moisture.

WARNINGS

1. In case of having following symptoms after using this, you're advised to stop using it immediately. If you keep using it, the symptoms will get worse and need to consult a dermatologist.
1) In case of having problems such as red rash, swollenness, itching, stimulation during usage.
2) In case of having the same symptoms above on the part you put this product on by direct sunlight.
2. You are banned to use it on the part where you have a scar, eczema, or dermatitis.
3. In case of getting it into your eyes, you have to wash it immediately.

KEEP OUT OF REACH OF CHILDREN

Keep out of the reach of babies and children.

INDICATIONS AND USAGE

1. Tighten the lid after using it.
2. Don't keep it in the place where the temperature is extremely hot or low and exposed the direct sunlight.
3. Please apply it an adequate quantity evenly on face and throat at the last stage of basic makeup.

DOSAGE AND ADMINISTRATION

Take up about 1.2g of it and smooth over the entire face.